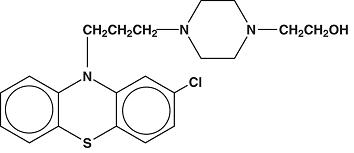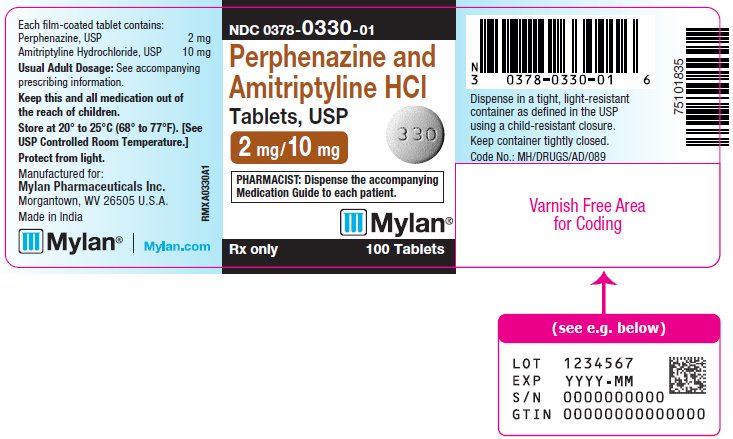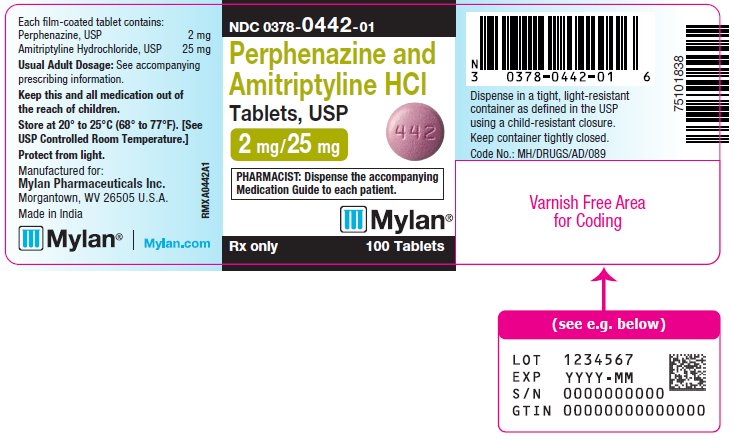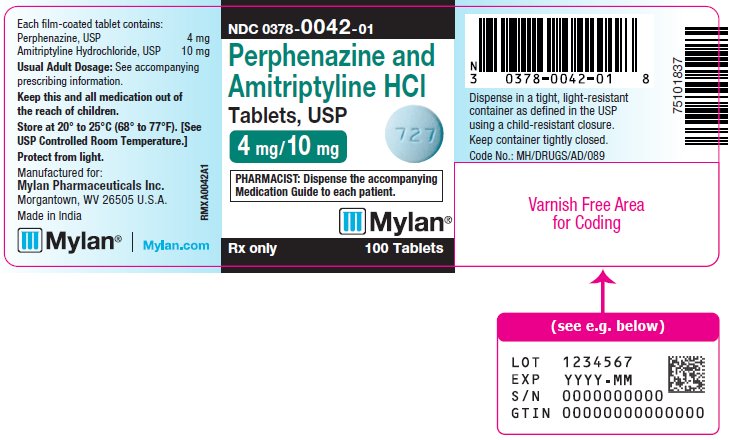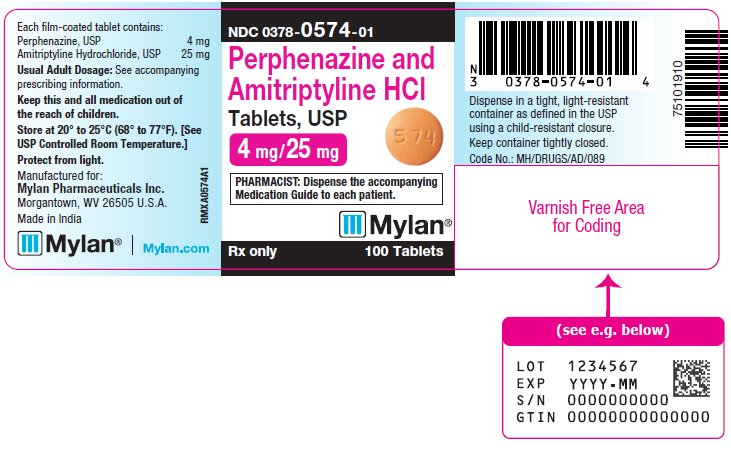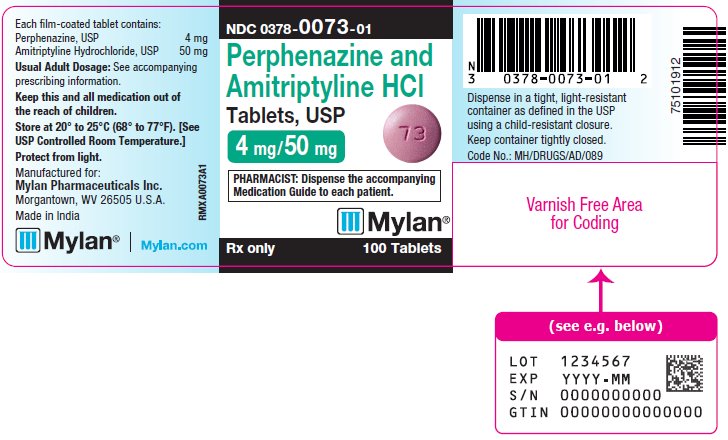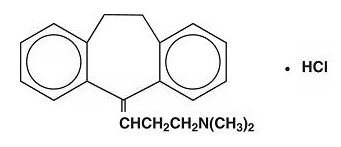 DRUG LABEL: Perphenazine and Amitriptyline Hydrochloride
NDC: 0378-0330 | Form: TABLET, FILM COATED
Manufacturer: Mylan Pharmaceuticals Inc.
Category: prescription | Type: HUMAN PRESCRIPTION DRUG LABEL
Date: 20250830

ACTIVE INGREDIENTS: PERPHENAZINE 2 mg/1 1; AMITRIPTYLINE HYDROCHLORIDE 10 mg/1 1
INACTIVE INGREDIENTS: SILICON DIOXIDE; CROSCARMELLOSE SODIUM; HYPROMELLOSE, UNSPECIFIED; MAGNESIUM STEARATE; MICROCRYSTALLINE CELLULOSE; POLYETHYLENE GLYCOL, UNSPECIFIED; STARCH, CORN; SODIUM LAURYL SULFATE; TITANIUM DIOXIDE; HYDROXYPROPYL CELLULOSE, UNSPECIFIED; CALCIUM SULFATE, UNSPECIFIED FORM; TALC

Perphenazine and Amitriptyline
Hydrochloride Tablets, USP
2 mg/10 mg, 2 mg/25 mg,
4 mg/10 mg, 4 mg/25 mg and 4 mg/50 mg

WARNING

Increased Mortality in Elderly Patients with Dementia-Related Psychosis

Elderly patients with dementia-related psychosis treated with antipsychotic drugs are at an increased risk of death. Analyses of seventeen placebo-controlled trials (modal duration of 10 weeks), largely in patients taking atypical antipsychotic drugs, revealed a risk of death in drug-treated patients of between 1.6 to 1.7 times the risk of death in placebo-treated patients. Over the course of a typical 10-week controlled trial, the rate of death in drug-treated patients was about 4.5%, compared to a rate of about 2.6% in the placebo group. Although the causes of death were varied, most of the deaths appeared to be either cardiovascular (e.g., heart failure, sudden death) or infectious (e.g., pneumonia) in nature. Observational studies suggest that, similar to atypical antipsychotic drugs, treatment with conventional antipsychotic drugs may increase mortality. The extent to which the findings of increased mortality in observational studies may be attributed to the antipsychotic drug as opposed to some characteristic(s) of the patients is not clear. Perphenazine and amitriptyline hydrochloride is not approved for the treatment of patients with dementia-related psychosis (see WARNINGS).

Suicidality and Antidepressant Drugs

Antidepressants increased the risk compared to placebo of suicidal thinking and behavior (suicidality) in children, adolescents and young adults in short-term studies of major depressive disorder (MDD) and other psychiatric disorders. Anyone considering the use of perphenazine and amitriptyline or any other antidepressant in a child, adolescent, or young adult must balance this risk with the clinical need. Short-term studies did not show an increase in the risk of suicidality with antidepressants compared to placebo in adults beyond age 24; there was a reduction in risk with antidepressants compared to placebo in adults aged 65 and older. Depression and certain other psychiatric disorders are themselves associated with increases in the risk of suicide. Patients of all ages who are started on antidepressant therapy should be monitored appropriately and observed closely for clinical worsening, suicidality, or unusual changes in behavior. Families and caregivers should be advised of the need for close observation and communication with the prescriber. Perphenazine and amitriptyline hydrochloride is not approved for use in pediatric patients. (See WARNINGS: Clinical Worsening and Suicide Risk, PRECAUTIONS: Information for Patients and PRECAUTIONS: Pediatric Use.)

DESCRIPTION

Perphenazine and amitriptyline hydrochloride, a broad spectrum psychotherapeutic agent for the management of outpatients and hospitalized patients with psychoses or neuroses characterized by mixtures of anxiety or agitation with symptoms of depression, is a combination of perphenazine and amitriptyline hydrochloride. Since such mixed syndromes can occur in patients with various degrees of intensity of mental illness, perphenazine and amitriptyline hydrochloride tablets are provided in multiple combinations to afford dosage flexibility for optimum management.

Perphenazine is a phenothiazine derivative. The formula is 4-[3-(2-chloro-10H-phenothiazin-10yl) propyl]-piperazineethanol. Perphenazine, USP is a white, odorless, bitter tasting powder that is insoluble in water. The molecular weight is 403.97. Its structural formula is:

Amitriptyline is a dibenzocycloheptadiene derivative. The formula is 10,11-dihydro-N,N-dimethyl-5H-dibenzo[a,d]cycloheptene-∆^5,γ -propylamine hydrochloride. Amitriptyline hydrochloride, USP is a white, odorless, crystalline compound which is freely soluble in water. The molecular weight is 313.87. Its structural formula is:

Each tablet for oral administration contains the following inactive ingredients: colloidal silicon dioxide, croscarmellose sodium, hypromellose, magnesium stearate, microcrystalline cellulose, polyethylene glycol, pregelatinized starch (corn), sodium lauryl sulfate and titanium dioxide.

The following additional product specific inactive ingredients are employed:

2 mg/10 mg - hydroxypropyl cellulose
2 mg/25 mg - hydroxypropyl cellulose
4 mg/10 mg - polysorbate 80
4 mg/25 mg - hydroxypropyl cellulose
4 mg/50 mg - hydroxypropyl cellulose

The following product specific coloring agents are employed:

2 mg/10 mg - calcium sulfate, talc
2 mg/25 mg - D&C Red No. 7 Calcium Lake, FD&C Blue No. 1 Aluminum Lake
4 mg/10 mg - FD&C Blue No. 1 Aluminum Lake
4 mg/25 mg - FD&C Yellow No. 6 Aluminum Lake
4 mg/50 mg - D&C Red No. 7 Calcium Lake, FD&C Blue No. 1 Aluminum Lake

CLINICAL PHARMACOLOGY

Perphenazine

In common with all members of the piperazine group of phenothiazine derivatives, perphenazine has greater behavioral potency than phenothiazine derivatives of other groups without a corresponding increase in autonomic, hematologic, or hepatic side effects.

Extrapyramidal effects, however, may occur more frequently. These effects are interpreted as neuropharmacologic. They usually regress after discontinuation of the drug.

Perphenazine is a potent tranquilizer and also a potent antiemetic. Orally, its milligram potency is about 5 or 6 times that of chlorpromazine with respect to behavioral effects. It is capable of alleviating symptoms of anxiety, tension, psychomotor excitement, and other manifestations of emotional stress without apparent dulling of mental acuity.

Amitriptyline Hydrochloride

Amitriptyline hydrochloride is an antidepressant with sedative effects. Its mechanism of action in man is not known. It is not a monoamine oxidase inhibitor and it does not act primarily by stimulation of the central nervous system.

INDICATIONS AND USAGE

Perphenazine and amitriptyline hydrochloride tablets are recommended for treatment of (1) patients with moderate to severe anxiety and/or agitation and depressed mood, (2) patients with depression in whom anxiety and/or agitation are severe, and (3) patients with depression and anxiety in association with chronic physical disease. In many of these patients, anxiety masks the depressive state so that, although therapy with a tranquilizer appears to be indicated, the administration of a tranquilizer alone will not be adequate.

Schizophrenic patients who have associated depressive symptoms should be considered for therapy with perphenazine and amitriptyline hydrochloride tablets.

CONTRAINDICATIONS

Perphenazine and amitriptyline hydrochloride tablets are contraindicated in depression of the central nervous system from drugs (barbiturates, alcohol, narcotics, analgesics, antihistamines); in the presence of evidence of bone marrow depression; and in patients known to be hypersensitive to phenothiazines or amitriptyline.

It should not be given concomitantly with monoamine oxidase inhibitors. Hyperpyretic crises, severe convulsions, and deaths have occurred in patients receiving tricyclic antidepressants and monoamine oxidase inhibitors simultaneously. When it is desired to replace a monoamine oxidase inhibitor with perphenazine and amitriptyline hydrochloride, a minimum of 14 days should be allowed to elapse after the former is discontinued. Perphenazine and amitriptyline hydrochloride should then be initiated cautiously with gradual increase in dosage until optimum response is achieved.

Amitriptyline hydrochloride is not recommended for use during the acute recovery phase following myocardial infarction.

WARNINGS

Increased Mortality in Elderly Patients with Dementia-Related Psychosis

Elderly patients with dementia-related psychosis treated with antipsychotic drugs are at an increased risk of death. Perphenazine and amitriptyline hydrochloride is not approved for the treatment of patients with dementia-related psychosis (see BOXED WARNING).

Clinical Worsening and Suicide Risk

Patients with major depressive disorder (MDD), both adult and pediatric, may experience worsening of their depression and/or the emergence of suicidal ideation and behavior (suicidality) or unusual changes in behavior, whether or not they are taking antidepressant medications, and this risk may persist until significant remission occurs. Suicide is a known risk of depression and certain other psychiatric disorders, and these disorders themselves are the strongest predictors of suicide. There has been a long-standing concern, however, that antidepressants may have a role in inducing worsening of depression and the emergence of suicidality in certain patients during the early phases of treatment. Pooled analyses of short-term placebo-controlled trials of antidepressant drugs (SSRIs and others) showed that these drugs increase the risk of suicidal thinking and behavior (suicidality) in children, adolescents, and young adults (ages 18 to 24) with major depressive disorder (MDD) and other psychiatric disorders. Short-term studies did not show an increase in the risk of suicidality with antidepressants compared to placebo in adults beyond age 24; there was a reduction with antidepressants compared to placebo in adults aged 65 and older.

The pooled analyses of placebo-controlled trials in children and adolescents with MDD, obsessive compulsive disorder (OCD), or other psychiatric disorders included a total of 24 short-term trials of nine antidepressant drugs in over 4,400 patients. The pooled analyses of placebo-controlled trials in adults with MDD or other psychiatric disorders included a total of 295 short-term trials (median duration of 2 months) of 11 antidepressant drugs in over 77,000 patients. There was considerable variation in risk of suicidality among drugs, but a tendency toward an increase in the younger patients for almost all drugs studied. There were differences in absolute risk of suicidality across the different indications, with the highest incidence in MDD. The risk differences (drug vs. placebo), however, were relatively stable within age strata and across indications. These risk differences (drug-placebo difference in the number of cases of suicidality per 1,000 patients treated) are provided in Table 1.

Table 1
Age Range | Drug-Placebo Difference in Number of Cases of Suicidality Per 1,000 Patients Treated
Increases Compared to Placebo
< 18 | 14 additional cases
18 to 24 | 5 additional cases
Decreases Compared to Placebo
25 to 64 | 1 fewer case
≥ 65 | 6 fewer cases

No suicides occurred in any of the pediatric trials. There were suicides in the adult trials, but the number was not sufficient to reach any conclusion about drug effect on suicide.

It is unknown whether the suicidality risk extends to longer-term use, i.e., beyond several months. However, there is substantial evidence from placebo-controlled maintenance trials in adults with depression that the use of antidepressants can delay the recurrence of depression.

All patients being treated with antidepressants for any indication should be monitored appropriately and observed closely for clinical worsening, suicidality and unusual changes in behavior, especially during the initial few months of a course of drug therapy, or at times of dose changes, either increases or decreases.

The following symptoms, anxiety, agitation, panic attacks, insomnia, irritability, hostility, aggressiveness, impulsivity, akathisia (psychomotor restlessness), hypomania, and mania, have been reported in adult and pediatric patients being treated with antidepressants for major depressive disorder as well as for other indications, both psychiatric and nonpsychiatric. Although a causal link between the emergence of such symptoms and either the worsening of depression and/or the emergence of suicidal impulses has not been established, there is concern that such symptoms may represent precursors to emerging suicidality.

Consideration should be given to changing the therapeutic regimen, including possibly discontinuing the medication, in patients whose depression is persistently worse, or who are experiencing emergent suicidality or symptoms that might be precursors to worsening depression or suicidality, especially if these symptoms are severe, abrupt in onset, or were not part of the patient's presenting symptoms.

Families and caregivers of patients being treated with antidepressants for major depressive disorder or other indications, both psychiatric and nonpsychiatric, should be alerted about the need to monitor patients for the emergence of agitation, irritability, unusual changes in behavior, and the other symptoms described above, as well as the emergence of suicidality, and to report such symptoms immediately to healthcare providers. Such monitoring should include daily observation by families and caregivers. Prescriptions for perphenazine and amitriptyline hydrochloride should be written for the smallest quantity of tablets consistent with good patient management, in order to reduce the risk of overdose.

Serotonin Syndrome

The development of a potentially life-threatening serotonin syndrome has been reported with tricyclic antidepressants, including perphenazine and amitriptyline hydrochloride tablets, alone but particularly with concomitant use of other serotonergic drugs (including triptans, tricyclic antidepressants, SSRI/SNRI, fentanyl, lithium, tramadol, tryptophan, buspirone, and St. John’s Wort) and with drugs that impair metabolism of serotonin (in particular, MAOIs, both those intended to treat psychiatric disorders and also others, such as linezolid and intravenous methylene blue). Serotonin syndrome symptoms may include mental status changes (e.g., agitation, hallucinations, delirium, and coma), autonomic instability (e.g., tachycardia, labile blood pressure, dizziness, diaphoresis, flushing, hyperthermia), neuromuscular changes (e.g., tremor, rigidity, myoclonus, hyperreflexia, incoordination), seizures, and/or gastrointestinal symptoms (e.g., nausea, vomiting, diarrhea). Patients should be monitored for the emergence of serotonin syndrome.

The concomitant use of perphenazine and amitriptyline hydrochloride tablets with MAOIs intended to treat psychiatric disorders is contraindicated. Perphenazine and amitriptyline hydrochloride tablets should also not be started in a patient who is being treated with MAOIs such as linezolid or intravenous methylene blue. All reports with methylene blue that provided information on the route of administration involved intravenous administration in the dose range of 1 mg/kg to 8 mg/kg. No reports involved the administration of methylene blue by other routes (such as oral tablets or local tissue injection) or at lower doses. There may be circumstances when it is necessary to initiate treatment with an MAOI such as linezolid or intravenous methylene blue in a patient taking perphenazine and amitriptyline hydrochloride tablets. Perphenazine and amitriptyline hydrochloride tablets should be discontinued before initiating treatment with the MAOI (see CONTRAINDICATIONS and DOSAGE AND ADMINISTRATION). If concomitant use of perphenazine and amitriptyline hydrochloride tablets with other serotonergic drugs, including triptans, tricyclic antidepressants, fentanyl, lithium, tramadol, buspirone, tryptophan, and St. John’s Wort is clinically warranted, patients should be made aware of a potential increased risk for serotonin syndrome, particularly during treatment initiation and dose increases. Treatment with perphenazine and amitriptyline hydrochloride tablets and any concomitant serotonergic agents should be discontinued immediately if the above events occur and supportive symptomatic treatment should be initiated.

Screening Patients for Bipolar Disorder

A major depressive episode may be the initial presentation of bipolar disorder. It is generally believed (though not established in controlled trials) that treating such an episode with an antidepressant alone may increase the likelihood of precipitation of a mixed/manic episode in patients at risk for bipolar disorder. Whether any of the symptoms described above represent such a conversion is unknown. However, prior to initiating treatment with an antidepressant, patients with depressive symptoms should be adequately screened to determine if they are at risk for bipolar disorder; such screening should include a detailed psychiatric history, including a family history of suicide, bipolar disorder, and depression. It should be noted that perphenazine and amitriptyline hydrochloride is not approved for use in treating bipolar depression.

Hyponatremia

Hyponatremia has occurred as a result of treatment with perphenazine and amitriptyline hydrochloride tablets. In many cases, hyponatremia appears to be the result of the syndrome of inappropriate antidiuretic hormone secretion (SIADH). Signs and symptoms of hyponatremia include headache, difficulty concentrating, memory impairment, confusion, weakness, and unsteadiness, which may lead to falls. Signs and symptoms associated with more severe and/or acute cases have included syncope, seizure, coma, respiratory arrest, and death.

In patients with symptomatic hyponatremia, discontinue perphenazine and amitriptyline hydrochloride tablets and institute appropriate medical intervention. Elderly patients, patients taking diuretics, and those who are volume-depleted may be at greater risk of developing hyponatremia with perphenazine and amitriptyline hydrochloride tablets.

Angle-Closure Glaucoma

The pupillary dilation that occurs following use of many antidepressant drugs including perphenazine and amitriptyline hydrochloride may trigger an angle closure attack in a patient with anatomically narrow angles who does not have a patent iridectomy.

Tardive Dyskinesia

Tardive dyskinesia, a syndrome consisting of potentially irreversible, involuntary, dyskinetic movements may develop in patients treated with neuroleptic (antipsychotic) drugs. Although the prevalence of the syndrome appears to be highest among the elderly, especially elderly women, it is impossible to rely upon prevalence estimates to predict, at the inception of neuroleptic treatment, which patients are likely to develop the syndrome. Whether neuroleptic drug products differ in their potential to cause tardive dyskinesia is unknown.

Both the risk of developing the syndrome and the likelihood that it will become irreversible are believed to increase as the duration of treatment and the total cumulative dose of neuroleptic drugs administered to the patient increase. However, the syndrome can develop, although much less commonly, after relatively brief treatment periods at low doses.

There is no known treatment for established cases of tardive dyskinesia, although the syndrome may remit, partially or completely, if neuroleptic treatment is withdrawn. Neuroleptic treatment, itself, however, may suppress (or partially suppress) the signs and symptoms of the syndrome and thereby may possibly mask the underlying disease process. The effect that symptomatic suppression has upon the long-term course of the syndrome is unknown.

Given these considerations, neuroleptics should be prescribed in a manner that is most likely to minimize the occurrence of tardive dyskinesia. Chronic neuroleptic treatment should generally be reserved for patients who suffer from a chronic illness that, 1) is known to respond to neuroleptic drugs, and, 2) for whom alternative, equally effective, but potentially less harmful treatments are not available or appropriate. In patients who do require chronic treatment, the smallest dose and the shortest duration of treatment producing a satisfactory clinical response should be sought. The need for continued treatment should be reassessed periodically.

If signs and symptoms of tardive dyskinesia appear in a patient on neuroleptics, drug discontinuation should be considered. However, some patients may require treatment despite the presence of the syndrome.

(For further information about the description of tardive dyskinesia and its clinical detection, please refer to the section on ADVERSE REACTIONS.)

Neuroleptic Malignant Syndrome (NMS)

A potentially fatal symptom complex sometimes referred to as Neuroleptic Malignant Syndrome (NMS) has been reported in association with antipsychotic drugs. Clinical manifestations of NMS are hyperpyrexia, muscle rigidity, altered mental status and evidence of autonomic instability (irregular pulse or blood pressure, tachycardia, diaphoresis, and cardiac dysrhythmias).

The diagnostic evaluation of patients with this syndrome is complicated. In arriving at a diagnosis, it is important to identify cases where the clinical presentation includes both serious medical illness (e.g., pneumonia, systemic infection, etc.) and untreated or inadequately treated extrapyramidal signs and symptoms (EPS). Other important considerations in the differential diagnosis include central anticholinergic toxicity, heat stroke, drug fever and primary central nervous system (CNS) pathology.

The management of NMS should include 1) immediate discontinuation of antipsychotic drugs and other drugs not essential to concurrent therapy, 2) intensive symptomatic treatment and medical monitoring, and 3) treatment of any concomitant serious medical problems for which specific treatments are available. There is no general agreement about specific pharmacological treatment regimens for uncomplicated NMS.

If a patient requires antipsychotic drug treatment after recovery from NMS, the potential reintroduction of drug therapy should be carefully considered. The patient should be carefully monitored, since recurrences of NMS have been reported.

Falls

Perphenazine and amitriptyline hydrochloride tablets may cause somnolence, postural hypotension, motor and sensory instability, which may lead to falls and, consequently, fractures or other injuries. For patients with diseases, conditions, or medications that could exacerbate these effects, complete fall risk assessments when initiating antipsychotic treatment and recurrently for patients on long-term antipsychotic therapy.

General

Perphenazine and amitriptyline hydrochloride should not be given concomitantly with guanethidine or similarly acting compounds, since amitriptyline, like other tricyclic antidepressants, may block the antihypertensive effect of these compounds.

Because of the atropine like activity of amitriptyline, this product should be used with caution in patients with a history of urinary retention or with angle-closure glaucoma. In patients with angle-closure glaucoma, even average doses may precipitate an attack.

It should be used with caution also in patients with convulsive disorders. Dosage of anticonvulsive agents may have to be increased.

Patients with cardiovascular disorders should be watched closely. Tricyclic antidepressants, including amitriptyline hydrochloride, particularly when given in high doses, have been reported to produce arrhythmias, sinus tachycardia, and prolongation of the conduction time. Myocardial infarction and stroke have been reported with drugs of this class.

Close supervision is required when amitriptyline hydrochloride is given to hyperthyroid patients or those receiving thyroid medication.

This product may enhance the response to alcohol and the effects of barbiturates and other CNS depressants. In patients who may use alcohol excessively, it should be borne in mind that the potentiation may increase the danger inherent in any suicide attempt or overdosage. Delirium has been reported with concurrent administration of amitriptyline and disulfiram.

Usage in Pregnancy

Perphenazine and amitriptyline hydrochloride is not recommended for use in pregnant patients or in nursing mothers at this time. Reproduction studies in rats have shown no fetal abnormalities; however, clinical experience and follow-up in pregnancy have been limited, and the possibility of adverse effects on fetal development must be considered.

Pregnancy

Nonteratogenic Effects

Neonates exposed to antipsychotic drugs, during the third trimester of pregnancy are at risk for extrapyramidal and/or withdrawal symptoms following delivery. There have been reports of agitation, hypertonia, hypotonia, tremor, somnolence, respiratory distress and feeding disorder in these neonates. These complications have varied in severity; while in some cases symptoms have been self-limited, in other cases neonates have required intensive care unit support and prolonged hospitalization.

Perphenazine and amitriptyline hydrochloride should be used during pregnancy only if the potential benefit justifies the potential risk to the fetus.

PRECAUTIONS

Leukopenia, Neutropenia, and Agranulocytosis

In clinical trial and postmarketing experience, events of leukopenia/neutropenia and agranulocytosis have been reported temporally related to antipsychotic agents.

Possible risk factors for leukopenia/neutropenia include preexisting low white blood cell count (WBC) and history of drug induced leukopenia/neutropenia. Patients with a preexisting low WBC or a history of drug induced leukopenia/neutropenia should have their complete blood count (CBC) monitored frequently during the first few months of therapy and should discontinue perphenazine and amitriptyline hydrochloride tablets at the first sign of a decline in WBC in the absence of other causative factors.

Patients with neutropenia should be carefully monitored for fever or other symptoms or signs of infection and treated promptly if such symptoms or signs occur. Patients with severe neutropenia (absolute neutrophil count < 1000/mm3) should discontinue perphenazine and amitriptyline hydrochloride tablets and have their WBC followed until recovery.

General

The possibility of suicide in depressed patients remains during treatment and until significant remission occurs. Such patients should not have access to large quantities of this drug.

Perphenazine

As with all phenothiazine compounds, perphenazine should not be used indiscriminately. Caution should be observed in giving it to patients who have previously exhibited severe adverse reactions to other phenothiazines.

Some of the untoward actions of perphenazine tend to appear more frequently when high doses are used. However, as with other phenothiazine compounds, patients receiving perphenazine in any dosage should be kept under close supervision.

The antiemetic effect of perphenazine may obscure signs of toxicity due to overdosage of other drugs, or render more difficult the diagnosis of disorders such as brain tumors or intestinal obstruction.

A significant, not otherwise explained, rise in body temperature may suggest individual intolerance to perphenazine, in which case this product should be discontinued.

Neuroleptic drugs elevate prolactin levels; the elevation persists during chronic administration. Tissue culture experiments indicate that approximately one-third of human breast cancers are prolactin dependent in vitro, a factor of potential importance if the prescription of these drugs is contemplated in a patient with a previously detected breast cancer. Although disturbances such as galactorrhea, amenorrhea, gynecomastia, and impotence have been reported, the clinical significance of elevated serum prolactin levels is unknown for most patients. An increase in mammary neoplasms has been found in rodents after chronic administration of neuroleptic drugs. Published epidemiologic studies have shown inconsistent results when exploring the association between hyperprolactinemia and breast cancer.

Amitriptyline Hydrochloride

Depressed patients, particularly those with known manic depressive illness, may experience a shift to mania or hypomania. Patients with paranoid symptomatology may have an exaggeration of such symptoms. The tranquilizing effect of this product seems to reduce the likelihood of these effects.

Both elevation and lowering of blood sugar levels have been reported.

Amitriptyline hydrochloride should be used with caution in patients with impaired liver functions.

Information for Patients

While on therapy with perphenazine and amitriptyline hydrochloride, patients should be advised as to the possible impairment of mental and/or physical abilities required for performance of hazardous tasks, such as operating machinery or driving a motor vehicle.

Prescribers or other health professionals should inform patients, their families, and their caregivers about the benefits and risks associated with treatment with perphenazine and amitriptyline hydrochloride and should counsel them in its appropriate use. A patient Medication Guide about “Antidepressant Medicines, Depression and other Serious Mental Illnesses and Suicidal Thoughts or Actions” is available for perphenazine and amitriptyline hydrochloride. The prescriber or health professional should instruct patients, their families, and their caregivers to read the Medication Guide and should assist them in understanding its contents. Patients should be given the opportunity to discuss the contents of the Medication Guide and to obtain answers to any questions they may have. The complete text of the Medication Guide is reprinted at the end of this document.

Patients should be advised of the following issues and asked to alert their prescriber if these occur while taking perphenazine and amitriptyline hydrochloride.

Patients should be advised that taking perphenazine and amitriptyline hydrochloride can cause mild pupillary dilation, which in susceptible individuals, can lead to an episode of angle-closure glaucoma. Pre-existing glaucoma is almost always open-angle glaucoma because angle-closure glaucoma, when diagnosed, can be treated definitively with iridectomy. Open-angle glaucoma is not a risk factor for angle-closure glaucoma. Patients may wish to be examined to determine whether they are susceptible to angle closure, and have a prophylactic procedure (e.g., iridectomy), if they are susceptible.

Clinical Worsening and Suicide Risk

Patients, their families and their caregivers should be encouraged to be alert to the emergence of anxiety, agitation, panic attacks, insomnia, irritability, hostility, aggressiveness, impulsivity, akathisia (psychomotor restlessness), hypomania, mania, other unusual changes in behavior, worsening of depression, and suicidal ideation, especially early during antidepressant treatment and when the dose is adjusted up or down. Families and caregivers of patients should be advised to look for the emergence of such symptoms on a day to day basis, since changes may be abrupt. Such symptoms should be reported to the patient's prescriber or health professional, especially if they are severe, abrupt in onset, or were not part of the patient's presenting symptoms. Symptoms such as these may be associated with an increased risk for suicidal thinking and behavior and indicate a need for very close monitoring and possibly changes in the medication.

Drug Interactions

Topiramate

Some patients may experience a large increase in amitriptyline concentration in the presence of topiramate and any adjustments in amitriptyline dose should be made according to the patient’s clinical response and not on the basis of plasma levels.

Drugs Metabolized by P450 2D6

The biochemical activity of the drug metabolizing isozyme cytochrome P450 2D6 (debrisoquin hydroxylase) is reduced in a subset of the Caucasian population (about 7% to 10% of Caucasians are so called "poor metabolizers"); reliable estimates of the prevalence of reduced P450 2D6 isozyme activity among Asian, African, and other populations are not yet available. Poor metabolizers have higher than expected plasma concentrations of tricyclic antidepressants (TCAs) when given usual doses. Depending on the fraction of drug metabolized by P450 2D6, the increase in plasma concentration may be small, or quite large (8-fold increase in plasma AUC of the TCA).

In addition, certain drugs inhibit the activity of this isozyme and make normal metabolizers resemble poor metabolizers. An individual who is stable on a given dose of TCA may become abruptly toxic when given one of these inhibiting drugs as concomitant therapy. The drugs that inhibit cytochrome P450 2D6 include some that are not metabolized by the enzyme (quinidine; cimetidine) and many that are substrates for P450 2D6 (many other antidepressants, phenothiazines, and the Type 1C antiarrhythmics propafenone and flecainide). While all the selective serotonin reuptake inhibitors (SSRIs), e.g., fluoxetine, sertraline, and paroxetine, inhibit P450 2D6, they may vary in the extent of inhibition. The extent to which SSRI TCA interactions may pose clinical problems will depend on the degree of inhibition and the pharmacokinetics of the SSRI involved. Nevertheless, caution is indicated in the coadministration of TCAs with any of the SSRIs and also in switching from one class to the other. Of particular importance, sufficient time must elapse before initiating TCA treatment in a patient being withdrawn from fluoxetine, given the long half-life of the parent and active metabolite (at least 5 weeks may be necessary).

Concomitant use of tricyclic antidepressants with drugs that can inhibit cytochrome P450 2D6 may require lower doses than usually prescribed for either the tricyclic antidepressant or the other drug. Furthermore, whenever one of these other drugs is withdrawn from cotherapy, an increased dose of tricyclic antidepressant may be required. It is desirable to monitor TCA plasma levels whenever a TCA is going to be coadministered with another drug known to be an inhibitor of P450 2D6.

Perphenazine

Patients on large doses of a phenothiazine drug who are undergoing surgery should be watched carefully for possible hypotensive phenomena. Moreover, reduced amounts of anesthetics or central nervous system depressants may be necessary.

Since phenothiazines and central nervous system depressants (opiates, analgesics, antihistamines, barbiturates) can potentiate each other, less than the usual dosage of the added drug is recommended and caution is advised when they are administered concomitantly.

Use with caution in patients who are receiving atropine or related drugs because of the additive anticholinergic effects and also in patients who will be exposed to extreme heat or organic phosphate insecticides.

The use of alcohol should be avoided, since additive effects and hypotension may occur. Patients should be cautioned that their response to alcohol may be increased while they are being treated with perphenazine and amitriptyline hydrochloride tablets. The risk of suicide and the danger of overdose may be increased in patients who use alcohol excessively due to the potentiation of the drug's effect.

Amitriptyline Hydrochloride

When amitriptyline hydrochloride is given with anticholinergic agents or sympathomimetic drugs, including epinephrine combined with local anesthetics, close supervision and careful adjustment of dosages are required.

Hyperpyrexia has been reported when amitriptyline is administered with anticholinergic agents or with neuroleptic drugs, particularly during hot weather.

Paralytic ileus may occur in patients taking tricyclic antidepressants in combination with anticholinergic type drugs.

This drug may enhance the response to alcohol and the effects of barbiturates and other CNS depressants.

Concurrent administration of amitriptyline hydrochloride and electroshock therapy may increase the hazards associated with such therapy. Such treatment should be limited to patients for whom it is essential.

Discontinue the drug several days before elective surgery, if possible.

Concurrent administration of cimetidine and tricyclic antidepressants can produce clinically significant increases in the plasma concentrations of the tricyclic antidepressant. Serious anticholinergic symptoms (severe dry mouth, urinary retention, blurred vision) have been associated with elevations in the serum levels of the tricyclic antidepressant when cimetidine is added to the drug regimen. Additionally, higher than expected steady-state serum concentrations of the tricyclic antidepressant have been observed when therapy is initiated in patients taking cimetidine.

Alternatively, decreases in the steady-state serum concentration of the tricyclic antidepressant have been reported in well controlled patients on concurrent therapy upon discontinuance of cimetidine. The therapeutic efficacy of the tricyclic antidepressant may be compromised in these patients as the cimetidine is discontinued.

Caution is advised if patients receive large doses of ethchlorvynol concurrently. Transient delirium has been reported in patients who were treated with 1 g of ethchlorvynol and 75 mg to 150 mg of amitriptyline hydrochloride.

Pediatric Use

Safety and effectiveness in the pediatric population have not been established (see BOX WARNING and WARNINGS: Clinical Worsening and Suicide Risk). Anyone considering the use of perphenazine and amitriptyline hydrochloride in a child or adolescent must balance the potential risks with the clinical need.

ADVERSE REACTIONS

To date, clinical evaluation of perphenazine has not revealed any adverse reactions peculiar to the combination. The adverse reactions that occurred were limited to those that have been reported previously for perphenazine and amitriptyline.

Treatment with perphenazine and amitriptyline hydrochloride is commonly associated with sedation, hypertension, neurological impairments and dry mouth.

Perphenazine

The common acute neurological effects of neuroleptic drugs, including perphenazine, consist of dystonia, akathisia or motor restlessness, and pseudoparkinsonism.

More chronic use of neuroleptics may be associated with the development of tardive dyskinesia. The salient features of this syndrome are described in the WARNINGS section and below.

The following adverse reactions have been reported and, within each category, are listed in order of decreasing severity.

Neurological

Tardive Dyskinesia

The syndrome is characterized by involuntary choreoathetoid movements which variously involve the tongue, face, mouth, lips, or jaw (e.g., protrusion of the tongue, puffing of cheeks, puckering of the mouth, chewing movements), trunk and extremities. The severity of the syndrome and the degree of impairment produced vary widely.

The syndrome may become clinically recognizable either during treatment, upon dosage reduction, or upon withdrawal of treatment. Movements may decrease in intensity and may disappear altogether if further treatment with neuroleptics is withheld. It is generally believed that reversibility is more likely after short rather than long term neuroleptic exposure. Consequently, early detection of tardive dyskinesia is important. To increase the likelihood of detecting the syndrome at the earliest possible time, the dosage of neuroleptic drug should be reduced periodically (if clinically possible) and the patient observed for signs of the disorder. It has been suggested that fine vermicular movements of the tongue may be an early sign of the syndrome, and that the full blown syndrome may not develop if medication is stopped when lingual vermiculation appears.

1. Dystonia: Class Effect: Symptoms of dystonia, prolonged abnormal contractions of muscle groups, may occur in susceptible individuals during the first few days of treatment. Dystonic symptoms include: spasm of the neck muscles, sometimes progressing to tightness of the throat, swallowing difficulty, difficulty breathing, and/or protrusion of the tongue. While these symptoms can occur at low doses, they occur more frequently and with greater severity with high potency and at higher doses of first generation antipsychotic drugs. An elevated risk of acute dystonia is observed in males and younger age groups.
2. Akathisia: Akathisia presents as constant motor restlessness. The patient with akathisia often complains, when asked, about his/her inability to stop moving. Akathisia should not be treated with an increased dose of neuroleptic; rather, the dose of antipsychotic may be lowered until the motor restlessness has subsided. The efficacy of anticholinergic treatment of this side effect is unestablished.
3. Pseudoparkinsonism: Pseudoparkinsonism refers to a drug-induced state similar to the classic syndrome. Generally, anticholinergic antiparkinsonian agents (i.e., benztropine, biperiden, procyclidine, or trihexphenidyl) and amantadine are helpful in alleviating symptoms that cannot be managed by neuroleptic dose reduction. The value of prophylactic antiparkinsonian drug therapy has not been established. The need for continued use of antiparkinsonian medication should be reevaluated periodically.

Cardiovascular

Hypotension, hypertension, tachycardia, peripheral edema, occasional change in pulse rate, ECG abnormalities (quinidine like effect), reversed epinephrine effect.

CNS and Neuromuscular

Extrapyramidal symptoms, including acute dyskinesia (see Neurological), reactivation of psychoses and production of catatonic like states, paradoxical excitement, ataxia, muscle weakness, hypnotic effects, mild insomnia, lassitude, headache, hyperflexia, altered cerebrospinal fluid proteins.

Autonomic: Urinary frequency or incontinence, dry mouth or salivation, nasal congestion.

Allergic: Anaphylactoid reactions, laryngeal edema, asthma, angioneurotic edema.

Hematologic: Blood dyscrasias including pancytopenia, agranulocytosis, leukopenia, thrombocytopenic purpura, eosinophilia.

Gastrointestinal: Liver damage (jaundice, biliary stasis), obstipation, vomiting, nausea, constipation, anorexia.

Dermatologic: Eczema up to exfoliative dermatitis, urticaria, erythema, itching, photosensitivity.

Ophthalmic: Pigmentation of the cornea and lens, blurred vision.

Endocrine: Lactation, galactorrhea, hyperglycemia, gynecomastia, disturbances in menstrual cycle.

Other: False positive pregnancy tests, including immunologic.

Other adverse reactions that should be considered because they have been reported with various phenothiazine compounds, but not with perphenazine, include:

CNS and Neuromuscular: Grand mal convulsions, cerebral edema.

Gastrointestinal: Polyphagia.

Dermatologic: Photophobia, pigmentation.

Ophthalmic: Pigmentary retinopathy.

Endocrine: Failure of ejaculation.

Amitriptyline Hydrochloride

Within each category the following adverse reactions are listed in order of decreasing severity. Included in the listing which follows are a few adverse reactions which have not been reported with this specific drug. However, pharmacological similarities among the tricyclic antidepressant drugs require that each of the reactions be considered when amitriptyline is administered.

Cardiovascular: Myocardial infarction, stroke, heart block, arrhythmias, hypotension, particularly orthostatic hypotension, hypertension, tachycardia, palpitation.

CNS and Neuromuscular: Coma, seizures, hallucinations, delusions, confusional states, disorientation, incoordination, ataxia, tremors, peripheral neuropathy, numbness, tingling and paresthesias of the extremities, extrapyramidal symptoms, dysarthria, disturbed concentration, excitement, anxiety, insomnia, restlessness, nightmares, drowsiness, dizziness, weakness, fatigue, headache, syndrome of inappropriate ADH (antidiuretic hormone) secretion, tinnitus, alteration in EEG patterns.

Anticholinergic: Paralytic ileus, hyperpyrexia, urinary retention, dilatation of urinary tract, constipation, blurred vision, disturbance of accommodation, increased intraocular pressure, mydriasis, dry mouth.

Allergic: Skin rash, urticaria, photosensitization, edema of face and tongue.

Hematologic: Bone marrow depression including agranulocytosis, leukopenia, thrombocytopenia, purpura, eosinophilia.

Gastrointestinal: Rarely hepatitis (including altered liver function and jaundice), nausea, epigastric distress, vomiting, anorexia, stomatitis, peculiar taste, diarrhea, parotid swelling, black tongue.

Endocrine: Testicular swelling and gynecomastia in the male, breast enlargement and galactorrhea in the female, increased or decreased libido, elevation and lowering of blood sugar levels.

Other: Alopecia, edema, weight gain or loss, urinary frequency, increased perspiration, and hyponatremia.

Withdrawal Symptoms

After prolonged administration, abrupt cessation of treatment may produce nausea, headache, and malaise. Gradual dosage reduction has been reported to produce, within 2 weeks, transient symptoms including irritability, restlessness, and dream and sleep disturbance. These symptoms are not indicative of addiction. Rare instances have been reported of mania or hypomania occurring within 2 to 7 days following cessation of chronic therapy with tricyclic antidepressants.

OVERDOSAGE*

Deaths may occur from overdosage with this class of drugs. Multiple drug ingestion (including alcohol) is common in deliberate overdose. As the management is complex and changing, it is recommended that the physician contact a poison control center for current information on treatment. Signs and symptoms of toxicity develop rapidly after overdose, therefore, hospital monitoring is required as soon as possible.

Manifestations

Overdosage of perphenazine and amitriptyline hydrochloride tablets may cause any of the adverse reactions listed for perphenazine or amitriptyline hydrochloride.

Overdosage of perphenazine usually produces extrapyramidal symptoms such as dyskinesia and dystonia as described under ADVERSE REACTIONS, but this may be masked by the anticholinergic effects of amitriptyline. Other symptoms may include stupor or coma; children may have convulsive seizures.

Critical manifestations of tricyclic antidepressant overdose includes: cardiac dysrhythmias, severe hypotension, convulsions, and CNS depression, including coma. Changes in the electrocardiogram, particularly in QRS axis or width, are clinically significant indicators of tricyclic antidepressant toxicity. Other signs of overdose may include: confusion, disturbed concentration, transient visual hallucinations, dilated pupils, agitation, hyperactive reflexes, stupor, drowsiness, muscle rigidity, vomiting, hypothermia, hyperpyrexia, or any of the symptoms listed under ADVERSE REACTIONS.

Management

General

Obtain an ECG and immediately initiate cardiac monitoring. Protect the patient's airway, establish an intravenous line, and initiate gastric decontamination. A minimum of 6 hours of observation with cardiac monitoring and observation for signs of CNS or respiratory depression, hypotension, cardiac dysrhythmias and/or conduction blocks, and seizures is necessary. If signs of toxicity occur at any time during this period, extended monitoring is required. There are case reports of patients succumbing to fatal dysrhythmias late after overdose; these patients had clinical evidence of significant poisoning prior to death and most received inadequate gastrointestinal decontamination. Monitoring of plasma drug levels should not guide management of the patient.

Gastrointestinal Decontamination

All patients suspected of tricyclic antidepressant overdose should receive gastrointestinal decontamination. This should include large volume gastric lavage followed by activated charcoal. If consciousness is impaired, the airway should be secured prior to lavage. Emesis is contraindicated.

Cardiovascular

A maximal limb lead QRS duration of ≥ 0.10 seconds may be the best indication of the severity of the overdose. Serum alkalinization, to a pH of 7.45 to 7.55, using intravenous sodium bicarbonate and hyperventilation (as needed) should be instituted for patients with dysrhythmias and/or QRS widening. A pH > 7.60 or a pCO2 < 20 mm Hg is undesirable. Dysrhythmias unresponsive to sodium bicarbonate therapy/hyperventilation may respond to lidocaine, bretylium, or phenytoin. Type 1A and 1C antiarrhythmics are generally contraindicated (e.g., quinidine, disopyramide, and procainamide).

In rare instances, hemoperfusion may be beneficial in acute refractory cardiovascular instability in patients with acute toxicity. However, hemodialysis, peritoneal dialysis, exchange transfusions, and forced diuresis generally have been reported as ineffective in tricyclic antidepressant poisoning.

CNS

In patients with CNS depression, early intubation is advised because of the potential for abrupt deterioration. Seizures should be controlled with benzodiazepines, or if these are ineffective, other anticonvulsants (e.g., phenobarbital, phenytoin). Physostigmine is not recommended except to treat life threatening symptoms that have been unresponsive to other therapies, and then only in consultation with a poison control center.

Psychiatric Follow-Up

Since overdosage is often deliberate, patients may attempt suicide by other means during the recovery phase. Psychiatric referral may be appropriate.

Pediatric Management

The principles of management of child and adult overdosages are similar. It is strongly recommended that the physician contact the local poison control center for specific pediatric treatment.

DOSAGE AND ADMINISTRATION

Since dosage for children has not been established, this product is not recommended for use in children.

The total daily dose of perphenazine and amitriptyline hydrochloride tablets should not exceed 16 mg of perphenazine and 200 mg of amitriptyline hydrochloride.

Initial Dosage

In psychoneurotic patients when anxiety and depression are of such a degree as to warrant combined therapy, one tablet of the 2 mg/25 mg or 4 mg/25 mg three or four times a day or one tablet of the 4 mg/50 mg combination twice a day is recommended.

In more severely ill patients with schizophrenia, the 4 mg/25 mg combination is recommended in an initial dose of two tablets three times a day. If necessary, a fourth dose may be given at bedtime.

In elderly patients and adolescents, and some other patients in whom anxiety tends to predominate, perphenazine and amitriptyline hydrochloride tablet 4 mg/10 mg combination may be administered three or four times a day initially, then adjusted as required for subsequent adequate therapy.

Maintenance Dosage

Depending on the condition being treated, therapeutic response may take from a few days to a few weeks or even longer. After a satisfactory response is noted, dosage should be reduced to the smallest amount necessary to obtain relief from the symptoms for which this product is being administered. A useful maintenance dosage is one tablet of the 2 mg/25 mg or 4 mg/25 mg combination two to four times a day or one tablet of the 4 mg/50 mg combination twice a day. Perphenazine and amitriptyline hydrochloride tablets, 2 mg/10 mg and 4 mg/10 mg can be used to increase flexibility in adjusting maintenance dosage to the lowest amount consistent with relief of symptoms. In some patients, maintenance dosage is required for many months.

HOW SUPPLIED

Perphenazine and Amitriptyline Hydrochloride Tablets, USP are available in the following combinations:

DOSAGE FORM
ACTIVE INGREDIENT
 | 2 mg/10 mg
Perphenazine, USP | 2
Amitriptyline hydrochloride, USP | 10
 | 2 mg/25 mg
Perphenazine, USP | 2
Amitriptyline hydrochloride, USP | 25
 | 4 mg/10 mg
Perphenazine, USP | 4
Amitriptyline hydrochloride, USP | 10
 | 4 mg/25 mg
Perphenazine, USP | 4
Amitriptyline hydrochloride, USP | 25
 | 4 mg/50 mg
Perphenazine, USP | 4
Amitriptyline hydrochloride, USP | 50

The 2 mg/10 mg combination tablets are white, film-coated, round, unscored tablets debossed with MYLAN on one side of the tablet and 330 on the other side. They are available as follows:

NDC 0378-0330-01
bottles of 100 tablets

The 2 mg/25 mg combination tablets are purple, film-coated, round, unscored tablets debossed with MYLAN on one side of the tablet and 442 on the other side. They are available as follows:

NDC 0378-0442-01
bottles of 100 tablets

The 4 mg/10 mg combination tablets are blue, film-coated, round, unscored tablets debossed with MYLAN on one side of the tablet and 727 on the other side. They are available as follows:

NDC 0378-0042-01
bottles of 100 tablets

The 4 mg/25 mg combination tablets are orange, film-coated, round, unscored tablets debossed with MYLAN on one side of the tablet and 574 on the other side. They are available as follows:

NDC 0378-0574-01
bottles of 100 tablets

The 4 mg/50 mg combination tablets are purple, film-coated, round, unscored tablets debossed with MYLAN on one side of the tablet and 73 on the other side. They are available as follows:

NDC 0378-0073-01
bottles of 100 tablets

Store at 20° to 25°C (68° to 77°F). [See USP Controlled Room Temperature.]

Protect from light.

Dispense in a tight, light-resistant container as defined in the USP using a child-resistant closure.

PHARMACIST: Dispense a Medication Guide with each prescription.

* Poisindex Toxicologic Management. Topic: Antidepressants, Tricyclic. Micromedex Inc. Vol 85.

Medication Guide

Antidepressant Medicines, Depression and Other Serious Mental Illnesses,
and Suicidal Thoughts or Actions

Read the Medication Guide that comes with your or your family member’s antidepressant medicine. This Medication Guide is only about the risk of suicidal thoughts and actions with antidepressant medicines. Talk to your, or your family member’s, healthcare provider about:

- all risks and benefits of treatment with antidepressant medicines
- all treatment choices for depression or other serious mental illness

What is the most important information I should know about antidepressant medicines, depression and other serious mental illnesses, and suicidal thoughts or actions?

1. Antidepressant medicines may increase suicidal thoughts or actions in some children, teenagers, and young adults within the first few months of treatment.
2. Depression and other serious mental illnesses are the most important causes of suicidal thoughts and actions. Some people may have a particularly high risk of having suicidal thoughts or actions. These include people who have (or have a family history of) bipolar illness (also called manic-depressive illness) or suicidal thoughts or actions.
3. How can I watch for and try to prevent suicidal thoughts and actions in myself or a family member?
  1. Pay close attention to any changes, especially sudden changes, in mood, behaviors, thoughts, or feelings. This is very important when an antidepressant medicine is started or when the dose is changed.
  2. Call the healthcare provider right away to report new or sudden changes in mood, behavior, thoughts, or feelings.
  3. Keep all follow-up visits with the healthcare provider as scheduled. Call the healthcare provider between visits as needed, especially if you have concerns about symptoms.

Call a healthcare provider right away if you or your family member has any of the following symptoms, especially if they are new, worse, or worry you:

- thoughts about suicide or dying
- attempts to commit suicide
- new or worse depression
- new or worse anxiety
- feeling very agitated or restless
- panic attacks
- trouble sleeping (insomnia)
- new or worse irritability
- acting aggressive, being angry, or violent
- acting on dangerous impulses
- an extreme increase in activity and talking (mania)

- other unusual changes in behavior or mood
- Low salt (sodium) levels in the blood. Elderly people may be at greater risk for this. Symptoms may include:
- headache
- weakness or feeling unsteady
- confusion, problems concentrating or thinking or memory problems
- Visual problems: eye pain, changes in vision, swelling or redness in or around the eye

- Serotonin Syndrome. This condition can be life-threatening and symptoms may include:
- agitation, hallucinations, coma, or other changes in mental status
- racing heartbeat, high or low blood pressure
- coordination problems or muscle twitching (overactive reflexes)
- nausea, vomiting, or diarrhea
- sweating or fever
- muscle rigidity

What else do I need to know about antidepressant medicines?

- Never stop an antidepressant medicine without first talking to a healthcare provider. Stopping an antidepressant medicine suddenly can cause other symptoms.
- Visual problems: Only some people are at risk for these problems. You may want to undergo an eye examination to see if you are at risk and receive preventative treatment if you are.
- Antidepressants are medicines used to treat depression and other illnesses. It is important to discuss all the risks of treating depression and also the risks of not treating it. Patients and their families or other caregivers should discuss all treatment choices with the healthcare provider, not just the use of antidepressants.
- Antidepressant medicines have other side effects. Talk to the healthcare provider about the side effects of the medicine prescribed for you or your family member.
- Antidepressant medicines can interact with other medicines. Know all of the medicines that you or your family member takes. Keep a list of all medicines to show the healthcare provider. Do not start new medicines without first checking with your healthcare provider.
- Not all antidepressant medicines prescribed for children are FDA approved for use in children. Talk to your child’s healthcare provider for more information.
- Tell your healthcare provider if have low sodium levels in your blood during treatment with perphenazine and amitriptyline hydrochloride tablets.

Call your doctor for medical advice about side effects. You may report side effects to FDA at 1-800-FDA-1088.

This Medication Guide has been approved by the U.S. Food and Drug Administration for all antidepressants.

Manufactured for:
Mylan Pharmaceuticals Inc.
Morgantown, WV 26505 U.S.A.

Manufactured by:
Mylan Laboratories Limited
Hyderabad — 500 096, India

75110210

Revised: 8/2025

MXA:PRAT:R4m

PRINCIPAL DISPLAY PANEL - 2 mg/10 mg

NDC 0378-0330-01

Perphenazine and
Amitriptyline HCl
Tablets, USP
2 mg/10 mg

PHARMACIST: Dispense the accompanying
Medication Guide to each patient.

Rx only 100 Tablets

Each film-coated tablet contains:
Perphenazine, USP 2 mg
Amitriptyline Hydrochloride, USP 10 mg

Usual Adult Dosage: See accompanying
prescribing information.

Keep this and all medication out of
the reach of children.

Store at 20° to 25°C (68° to 77°F). [See
USP Controlled Room Temperature.]

Protect from light.

Manufactured for:
Mylan Pharmaceuticals Inc.
Morgantown, WV 26505 U.S.A.

Made in India

Mylan.com

RMXA0330A1

Dispense in a tight, light-resistant
container as defined in the USP
using a child-resistant closure.

Keep container tightly closed.

Code No.: MH/DRUGS/AD/089

PRINCIPAL DISPLAY PANEL - 2 mg/25 mg

NDC 0378-0442-01

Perphenazine and
Amitriptyline HCl
Tablets, USP
2 mg/25 mg

PHARMACIST: Dispense the accompanying
Medication Guide to each patient.

Rx only 100 Tablets

Each film-coated tablet contains:
Perphenazine, USP 2 mg
Amitriptyline Hydrochloride, USP 25 mg

Usual Adult Dosage: See accompanying
prescribing information.

Keep this and all medication out of
the reach of children.

Store at 20° to 25°C (68° to 77°F). [See
USP Controlled Room Temperature.]

Protect from light.

Manufactured for:
Mylan Pharmaceuticals Inc.
Morgantown, WV 26505 U.S.A.

Made in India

Mylan.com

RMXA0442A1
Dispense in a tight, light-resistant
container as defined in the USP
using a child-resistant closure.

Keep container tightly closed.

Code No.: MH/DRUGS/AD/089

PRINCIPAL DISPLAY PANEL - 4 mg/10 mg

NDC 0378-0042-01

Perphenazine and
Amitriptyline HCl
Tablets, USP
4 mg/10 mg

PHARMACIST: Dispense the accompanying
Medication Guide to each patient.

Rx only 100 Tablets

Each film-coated tablet contains:
Perphenazine, USP 4 mg
Amitriptyline Hydrochloride, USP 10 mg

Usual Adult Dosage: See accompanying
prescribing information.

Keep this and all medication out of
the reach of children.

Store at 20° to 25°C (68° to 77°F). [See
USP Controlled Room Temperature.]

Protect from light.

Manufactured for:
Mylan Pharmaceuticals Inc.
Morgantown, WV 26505 U.S.A.

Made in India

Mylan.com

RMXA0042A1

Dispense in a tight, light-resistant
container as defined in the USP
using a child-resistant closure.

Keep container tightly closed.

Code No.: MH/DRUGS/AD/089

PRINCIPAL DISPLAY PANEL - 4 mg/25 mg

NDC 0378-0574-01

Perphenazine and
Amitriptyline HCl
Tablets, USP
4 mg/25 mg

PHARMACIST: Dispense the accompanying
Medication Guide to each patient.

Rx only 100 Tablets

Each film-coated tablet contains:
Perphenazine, USP 4 mg
Amitriptyline Hydrochloride, USP 25 mg

Usual Adult Dosage: See accompanying
prescribing information.

Keep this and all medication out of
the reach of children.

Store at 20° to 25°C (68° to 77°F). [See
USP Controlled Room Temperature.]

Protect from light.

Manufactured for:
Mylan Pharmaceuticals Inc.
Morgantown, WV 26505 U.S.A.

Made in India

Mylan.com

RMXA0574A1

Dispense in a tight, light-resistant
container as defined in the USP
using a child-resistant closure.

Keep container tightly closed.

Code No.: MH/DRUGS/AD/089

PRINCIPAL DISPLAY PANEL - 4 mg/50 mg

NDC 0378-0073-01

Perphenazine and
Amitriptyline HCl
Tablets, USP
4 mg/50 mg

PHARMACIST: Dispense the accompanying
Medication Guide to each patient.

Rx only 100 Tablets

Each film-coated tablet contains:
Perphenazine, USP 4 mg
Amitriptyline Hydrochloride, USP 50 mg

Usual Adult Dosage: See
accompanying prescribing
information.

Keep this and all medication out of
the reach of children.

Store at 20° to 25°C (68° to 77°F). [See
USP Controlled Room Temperature.]

Protect from light.

Manufactured for:
Mylan Pharmaceuticals Inc.
Morgantown, WV 26505 U.S.A.

Made in India

Mylan.com

RMXA0073A1

Dispense in a tight, light-resistant
container as defined in the USP
using a child-resistant closure.

Keep container tightly closed.

Code No.: MH/DRUGS/AD/089